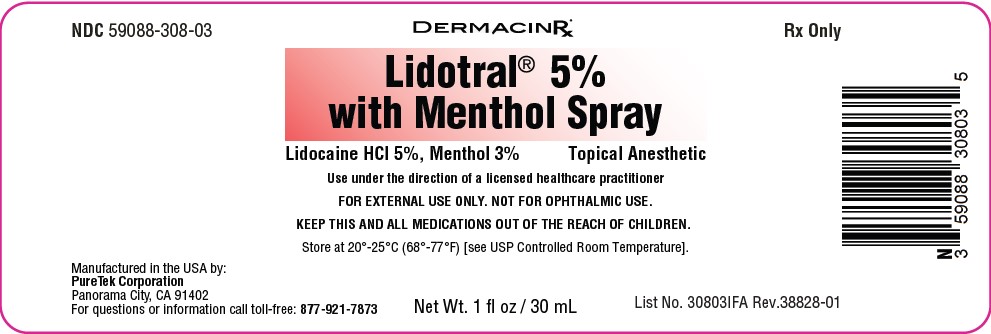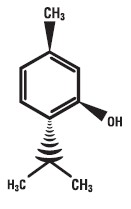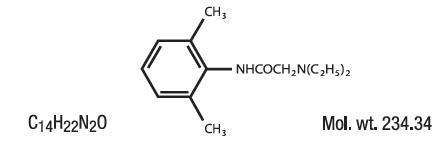 DRUG LABEL: Lidotral Five Percent with Menthol
NDC: 59088-308 | Form: LIQUID
Manufacturer: PureTek Corporation
Category: prescription | Type: HUMAN PRESCRIPTION DRUG LABEL
Date: 20241127

ACTIVE INGREDIENTS: MENTHOL 30 mg/1 mL; LIDOCAINE HYDROCHLORIDE 50 mg/1 mL
INACTIVE INGREDIENTS: WATER; AMINOMETHYLPROPANOL; ROSEMARY OIL; ACRYLATES/C10-30 ALKYL ACRYLATE CROSSPOLYMER (60000 MPA.S); BENZYL ALCOHOL; ALCOHOL; POLYETHYLENE GLYCOL 400

Lidotral 5% with Menthol Spray

DESCRIPTION

Lidotral™ 5% with Menthol Spray contains Lidocaine HCl 5% and Menthol 3% in a vehicle of Acrylates/C10-30 Alkyl Acrylate Crosspolymer, Aminomethyl Propanol, Aqua (Purified Water), Benzyl Alcohol, Ethyl Alcohol, PEG-8, Rosmarinus Officinalis (Rosemary) Leaf Oil, Fragrance.
Lidocaine is chemically designated as acetamide, 2-(diethylamino)-N-(2,6-dimethylphenyl), and has the following structure:

Menthol is chemically designed as (1R,2S,5R)-5-methyl-2-(propan-2-yl)cyclohexan-1-ol, and has the following structure:

Lidocaine 5% and Menthol 3% is a combination of ingredients with analgesics and anesthetic properties used in a unique way to maximize its pain-relieving effects to aid in addition to other therapies. This offers long lasting relief for a variety of pain conditions.

INDICATIONS

For the temporary relief of pain and itching associated with minor burns, sunburn, minor cuts, scrapes, insect bites, and minor skin irritation. This formulation can be used to assist patients in the treatment of mild to moderate acute or chronic aches or pain. Muscle or joint pain can be due to musculoligamentous strains, simple backache, tendonitis, osteoarthritis, rheumatoid arthritis, peripheral neuropathies such as diabetic neuropathy or post herpetic neuralgia, and other complex regional pains. If consulted by your physician, it may be used for other conditions as well. If consulted by your physician, it may be used for other conditions as well.

CLINICAL PHARMACOLOGY

Pharmacodynamics
Lidocaine is a common local anesthetic that relieves itching, burning, and pain. Topically, it blocks both initiation and conduction or nerve impulses by decreasing ionic flux through the neuronal membrane. Since it penetrates the skin, it creates an anesthetic effect by not just preventing pain signals from propagating to the brain out by stopping them before
they begin.
Menthol has some local anesthetic and counter irritant qualities and acts as a weak kappa opioid receptor agonist making it an analgesic as well, its ability to chemically trigger the cold-sensitive TRPM8 receptors in the skin is responsible for its cooling sensation when applied to the skin. Lastly, it enhances the efficacy of other topical applications by increasing penetration via vasodilation.

Pharmacokinetics

Absorption:
Lidocaine- Lidocaine may be absorbed following topical administration to mucous membranes, its rate and extent of absorption depending upon the specific site of application, duration of exposure, concentration and total dosage. In general, the rate of absorption of local anesthetic agents following topical application occurs most rapidly after intratracheal administration. Lidocaine is also well-absorbed from the gastrointestinal tract, but little intact drug appears in the circulation because of biotransformation in the liver. Lidocaine is metabolized rapidly by the liver and metabolites and unchanged drug are excreted by the kidneys. Biotransformation includes oxidative N-dealkylation, ring hydroxylation, cleavage of the amide linkage and conjugation. N-dealkylation, a major pathway of biotransformation, yields the metabolites monoethylglycinexylidide and glycinexylidide. The pharmacological/ toxicological actions of these metabolites are similar to, but less potent than, those of lidocaine. Approximately 90% of lidocaine administered is excreted in the form of various metabolites and less than 10% is excreted unchanged. The primary metabolite in urine is a conjugate of 4-hydroxy-2, 6-dimethylaniline. The plasma binding of lidocaine is dependent on drug concentration and the fraction bound decreases with increasing concentration. At concentrations of 1 to 4 g of free base per mL, 60 to 80 percent of lidocaine is protein bound. Binding is also dependent on the plasma concentration of the alpha-1-acid glycoprotein. Lidocaine crosses the blood-brain and placental barriers, presumably by passive diffusion. Studies of lidocaine metabolism following intravenous bolus injections have shown that the elimination half-life of this agent is typically 1.5 to 2 hours. Because of the rapid rate at which lidocaine is metabolized, any condition that affects liver function may alter lidocaine kinetics. The half-life may be prolonged two-fold or more in patients with liver dysfunction. Renal dysfunction does not affect lidocaine kinetics, but may increase the accumulation of metabolites. Factors such as acidosis and the use of CNS stimulants and depressants affect the CNS levels of lidocaine required to produce overt systemic effects. Objective adverse manifestations become increasingly apparent with increasing venous plasma levels above 6 g free base per mL. In the rhesus monkey, arterial blood levels of 18-21 g/mL have been shown to be threshold for convulsive activity.
Excretion:
Lidocaine- Lidocaine and its metabolites are excreted by the kidneys. Less than 10% of lidocaine is excreted unchanged. The half-life of lidocaine elimination from the plasma following IV administration is 81 to 149 minutes (mean 107 ± 22 SD, n = 15). The systemic clearance is 0.33 to 0.90 L/min (mean 0.64 ± 0.18 SD, n = 15).

CONTRAINDICATIONS

Lidotral™ 5% with Menthol Spray is contraindicated in patients with a known history of sensitivity to local anesthetics of the amide type, or to any other component of the product.

WARNINGS

For external use only. Not for ophthalmic use.

EXCESSIVE DOSING
Excessive dosing by applying Lidotral™ 5% with Menthol Spray to larger areas or for longer than the recommended wearing time could result in increased absorption of lidocaine and high blood concentrations, leading to serious adverse effects (see ADVERSE REACTIONS, Systemic Reactions). Lidocaine toxicity could be expected at lidocaine blood concentrations above 5 mcg/mL. The blood concentration of lidocaine is determined by the rate of systemic absorption and elimination. Longer duration of application, application of more than the recommended number of patches, smaller patients, or impaired elimination may all contribute to increasing the blood concentration of lidocaine. With recommended dosing, the average peak blood concentration is about 0.13 mcg/ mL, but concentrations higher than 0.25 mcg/mL have been observed in some individuals.

PRECAUTIONS

Allergic Reactions: Patients allergic to para-aminobenzoic acid derivatives (procaine, tetracaine, benzocaine, etc.) have not shown cross sensitivity to lidocaine. However, Lidotral™ 5% with Menthol Spray should be used with caution in patients with a history of drug sensitivities, especially if the etiologic agent is uncertain.

Non-intact Skin: Application to broken or inflamed skin, although not tested, may result in higher blood concentrations of lidocaine from increased absorption. Lidotral™ 5% with Menthol Spray is only recommended for use on intact skin.

External Heat Sources: Placement of external heat sources, such as heating pads or electric blankets, over Lidotral™ 5% with Menthol Spray is not recommended as this has not been evaluated and may increase plasma lidocaine levels.

Eye Exposure: The contact of Lidotral™ 5% with Menthol Spray with eyes, although not studied, should be avoided based on the findings of severe eye irritation with the use of similar products in animals. If eye contact occurs, immediately wash out the eye with water or saline and protect the eye until sensation returns.

Drug Interactions

Antiarrhythmic Drugs: Lidotral™ 5% with Menthol Spray should be used with caution in patients receiving Class I antiarrhythmic drugs (such as tocainide and mexiletine) since the toxic effects are additive and potentially synergistic.
Local Anesthetics: When Lidotral™ 5% with Menthol Spray is used concomitantly with other products containing local anesthetic agents, the amount absorbed from all formulations must be considered.

Carcinogenesis, Mutagenesis, Impairment of Fertility

Carcinogenesis: A minor metabolite, 2,6-xylidine, has been found to be carcinogenic in rats. The blood concentration of this metabolite is negligible following application of lidocaine.
Mutagenesis: Lidocaine HCl is not mutagenic in Salmonella/mammalian microsome test nor clastogenic in chromosome aberration assay with human lymphocytes and mouse micronucleus test.
Impairment of Fertility: The effect of lidocaine on fertility has not been studied.

Pregnancy

Teratogenic Effects: Pregnancy Category B. Lidocaine has not been studied in pregnancy. Reproduction studies with lidocaine have been performed in rats at doses up to 30 mg/kg subcutaneously and have revealed no evidence of harm to the fetus due to lidocaine. There are, however, no adequate and well- controlled studies in pregnant women. Because animal reproduction studies are not always predictive of human response, lidocaine should be used during pregnancy only if clearly needed.
Labor and Delivery
Lidocaine has not been studied in labor and delivery. Lidocaine is not contraindicated in labor and delivery. Should lidocaine be used concomitantly with other products containing lidocaine, total doses contributed by all formulations must be considered.

Nursing Mothers

Lidocaine has not been studied in nursing mothers. Lidocaine is excreted in human milk, and the milk: plasma ratio of lidocaine is 0.4. Caution should be exercised when lidocaine is administered to a nursing woman.

Pediatric Use

Safety and effectiveness in pediatric patients have not been established.

ADVERSE REACTIONS

Application Site Reactions
Even though adverse reactions are rare, a very small percentage of patients experience an unpleasant burning sensation, redness, warmth, or stinging. It is advisable to apply a small amount on the forearm prior to first use. If any of these effects persists or worsens, contact your physician or pharmacist immediately. This medication is not absorbed systemically but if any serious side effects (i.e. rash, itching/swelling, severe dizziness) are experienced, discontinue use immediately and contact your pharmacist or physician. This is not a complete list of all side effects that may occur. You may report side effects to the FDA at 800-FDA-1088 or at http://www.fda.gov/medwatch.
Allergic Reactions
Allergic and anaphylactoid reactions associated with lidocaine, although rare, can occur. They are characterized by angioedema, bronchospasm, dermatitis, dyspnea, hypersensitivity, laryngospasm, pruritus, shock, and urticaria. If they occur, they should be managed by conventional means. The detection of sensitivity by skin testing is of doubtful value.
Other Adverse Events
Due to the nature and limitation of spontaneous reports in post marketing surveillance, causality has not been established for additional reported adverse events including: Asthenia, confusion, disorientation, dizziness, headache, hyperesthesia, hypoesthesia, lightheadedness, metallic taste, nausea, nervousness, pain exacerbated, paresthesia, somnolence, taste alteration, vomiting, visual disturbances such as blurred vision, flushing, tinnitus, and tremor.
Systemic (Dose-Related) Reactions
Systemic adverse reactions following appropriate use of lidocaine is unlikely, due to the small dose absorbed (see CLINICAL PHARMACOLOGY, Pharmacokinetics). Systemic adverse effects of lidocaine are similar in nature to those observed with other amide local anesthetic agents, including CNS excitation and/or depression (light-headedness, nervousness, apprehension, euphoria, confusion, dizziness, drowsiness, tinnitus, blurred or double vision, vomiting, sensations of heat, cold or numbness, twitching, tremors, convulsions, unconsciousness, respiratory depression and arrest). Excitatory CNS reactions may be brief or not occur at all, in which case the first manifestation may be drowsiness merging into unconsciousness. Cardiovascular manifestations may include bradycardia, hypotension and cardiovascular collapse leading to arrest.
To report SUSPECTED ADVERSE REACTIONS, contact Actavis at 1-800- 272-5525 or FDA at 1-800-FDA-1088 or
www.fda.gov/medwatch for voluntary reporting of adverse reactions.

OVERDOSAGE

Lidocaine overdose from cutaneous absorption is rare, but could occur. If there is any suspicion of lidocaine overdose (see ADVERSE REACTIONS, Systemic Reactions), drug blood concentration should be checked. The management of overdose includes close monitoring, supportive care, and symptomatic treatment. Dialysis is of negligible value in the treatment of acute overdose with lidocaine.
In the absence of massive topical overdose or oral ingestion, evaluation of symptoms of toxicity should include consideration of other etiologies for the clinical effects, or over dosage from other sources of lidocaine or other local anesthetics.
The oral LD50 of lidocaine HCl is 459 (346 to 773) mg/kg (as the salt) in non-fasted female rats and 214 (159 to 324) mg/kg (as the salt) in fasted female rats, which are equivalent to roughly 4000 mg and 2000 mg, respectively, in a 60 to 70 kg man based on the equivalent surface area dosage conversion factors between species.

DOSAGE AND ADMINISTRATION

Spray to the affected area two or three times daily or as directed by a physician.
Apply Lidotral™ 5% with Menthol Spray to intact skin to cover the most painful area. Smaller areas of treatment are recommended in a debilitated patient, or a patient with impaired elimination.
When Lidotral™ 5% with Menthol Spray is used concomitantly with other products containing local anesthetic agents, the amount absorbed from all formulations must be considered.

HOW SUPPLIED

Lidotral™ 5% with Menthol Spray (Lidocaine HCl and Menthol)
1 fl. oz. NDC 59088-308-03
Store at 20° to 25°C (68° to 77°F) [See USP Controlled Room Temperature].